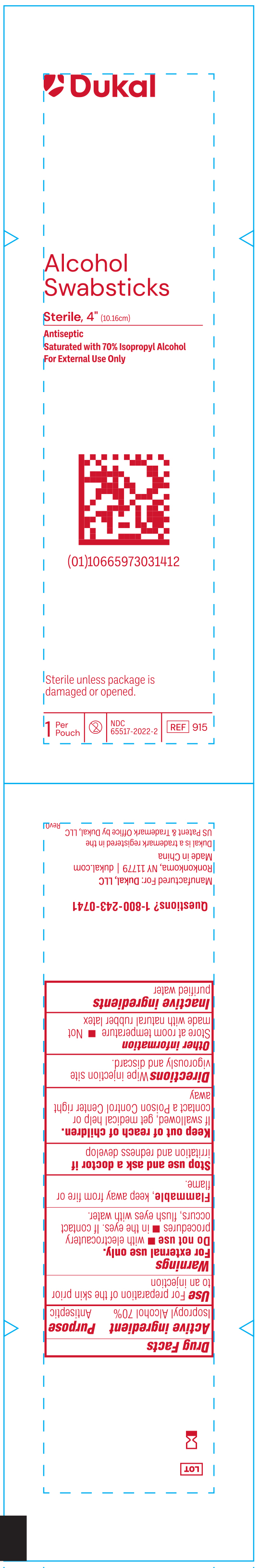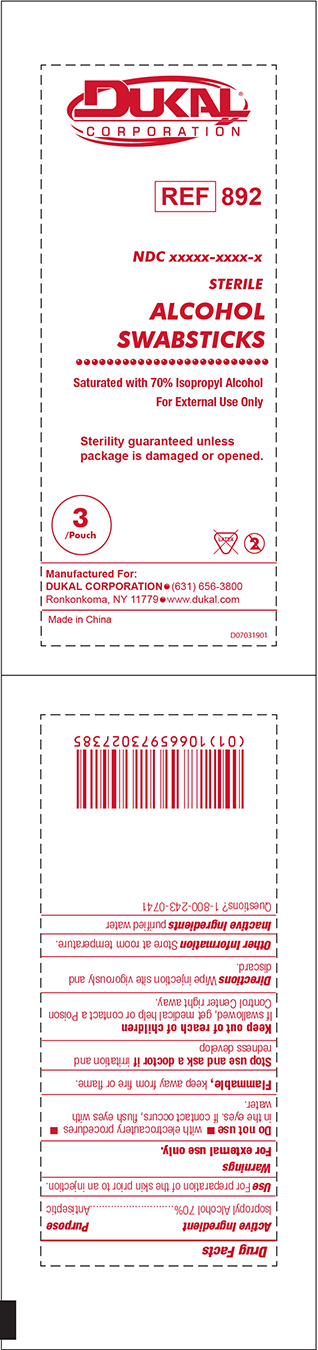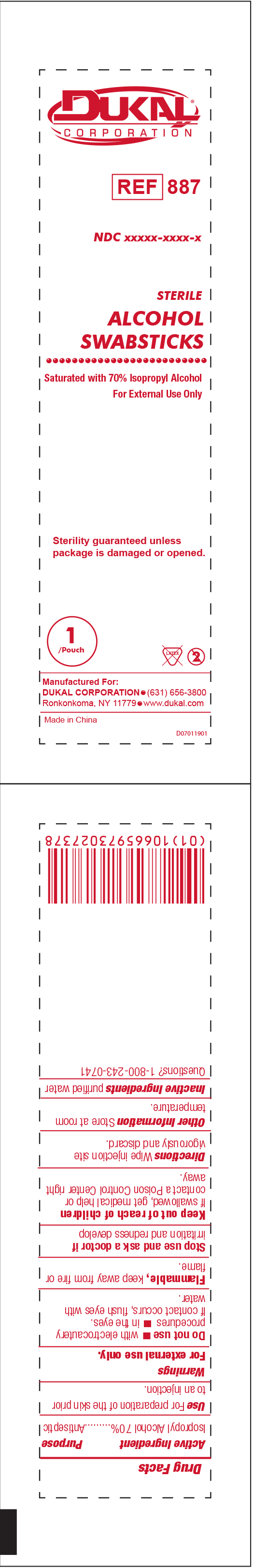 DRUG LABEL: Dukal Sterile Alcohol Swabstick
NDC: 65517-2022 | Form: SWAB
Manufacturer: Dukal LLC
Category: otc | Type: HUMAN OTC DRUG LABEL
Date: 20251119

ACTIVE INGREDIENTS: ISOPROPYL ALCOHOL 0.7 mL/1 mL
INACTIVE INGREDIENTS: WATER

65517-2022

Drug Facts

Active Ingredients

Isopropyl Alcohol 70%

Purpose

Antiseptic

Use

For Preparation of Skin prior to an injection

INDICATIONS AND USAGE

Wipe injection site vigorously and discard

Warnings

- For External Use Only
- Flammable, Keep away from fire or flame

Do Not Use

- with electrocautery procedures
- In the Eyes. If contact occurs, flush eyes with water

Stop Use

If irritation and redness develop. If condition persists, consult your health care practitioner.

Keep out of reach of children

If swallowed, get medical help or contact a Poison Control Center right away.

Other Information

Store at Room Temperature 15 - 30 C (59 - 86 F)

Other Information

Store at Room Temperature 15 - 30 C (59 - 86 F)

Inactive Ingredient

purified water

PACKAGE LABEL

Dukal Corporation

Ref 887

NDC 65517-2022-1

Sterile

ALCOHOL

SWABSTICKS

Saturated with 70% Isopropyl Alcohol

For External Use Only

Sterility guaranteed unless package is damaged or opened.

1 / Pouch Latex 2

Manufactured For:

Dukal Corporation 631-656-3800

Ronkonkoma, NY 11779 www.dukal.com

Made in China

PACKAGE LABEL

Dukal Corporation

Ref 892

NDC 65517-2022-3

Sterile

ALCOHOL

SWABSTICKS

Saturated with 70% Isopropyl Alcohol

For External Use Only

Sterility guaranteed unless package is damaged or opened.

3 / Pouch Latex 2

Manufactured For:

Dukal Corporation 631-656-3800

Ronkonkoma, NY 11779 www.dukal.com

Made in China

PACKAGE LABEL

Dukal

Alcohol

Swabsticks

Sterile, 4" (10.16cm)

Antiseptic

Saturated with 0% Isopropyl Alcohol

(01)10665973031412

Sterile unless package is damaged or opened

1 Per Pouch/2/NDC 65517-2022-2/Ref 915